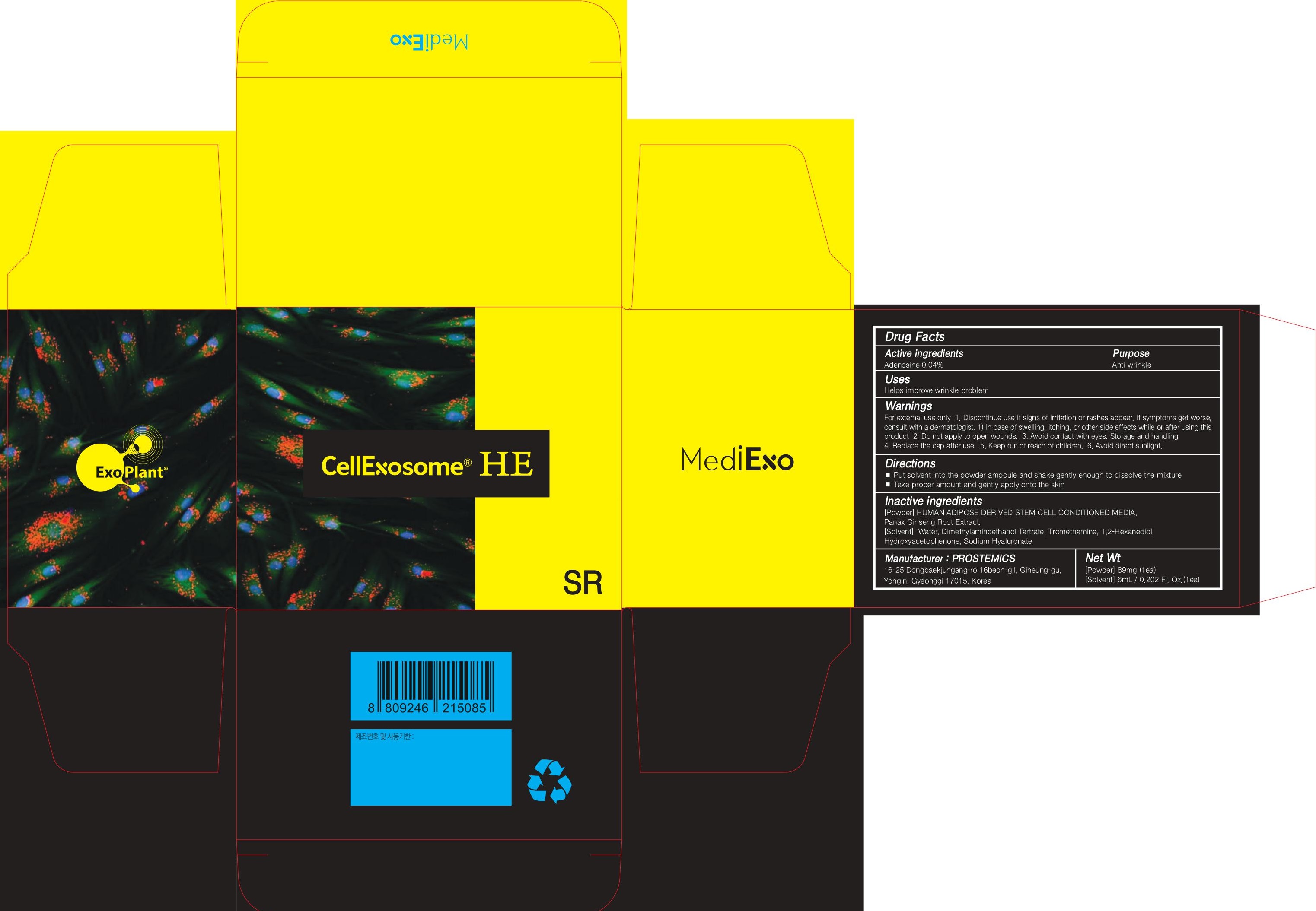 DRUG LABEL: CellExosome HE SR
NDC: 62041-300 | Form: LIQUID
Manufacturer: PROSTEMICS Co., Ltd.
Category: otc | Type: HUMAN OTC DRUG LABEL
Date: 20200214

ACTIVE INGREDIENTS: Adenosine 0.002 g/6 mL
INACTIVE INGREDIENTS: Water; DEANOL BITARTRATE

ACTIVE INGREDIENT

Active ingredients: Adenosine 0.04%

INACTIVE INGREDIENT

Inactive ingredients:

[Powder] HUMAN ADIPOSE DERIVED STEM CELL CONDITIONED MEDIA, Panax Ginseng Root Extract.
[Solvent] Water, Dimethylaminoethanol Tartrate, Tromethamine, 1,2-Hexanediol, Hydroxyacetophenone, Sodium Hyaluronate

PURPOSE

Purpose: Anti wrinkle

WARNINGS

For external use only
1. Discontinue use if signs of irritation or rashes appear. If symptoms get worse, consult with a dermatologist. 1) In case of swelling, itching, or other side effects while or after using this product
2. Do not apply to open wounds.
3. Avoid contact with eyes.
Storage and handling
4. Replace the cap after use
5. Keep out of reach of children.
6. Avoid direct sunlight.

KEEP OUT OF REACH OF CHILDREN SECTION

Uses

Helps improve wrinkle problem

Directions

■ Put solvent into the powder ampoule and shake gently enough to dissolve the mixture
■ Take proper amount and gently apply onto the skin